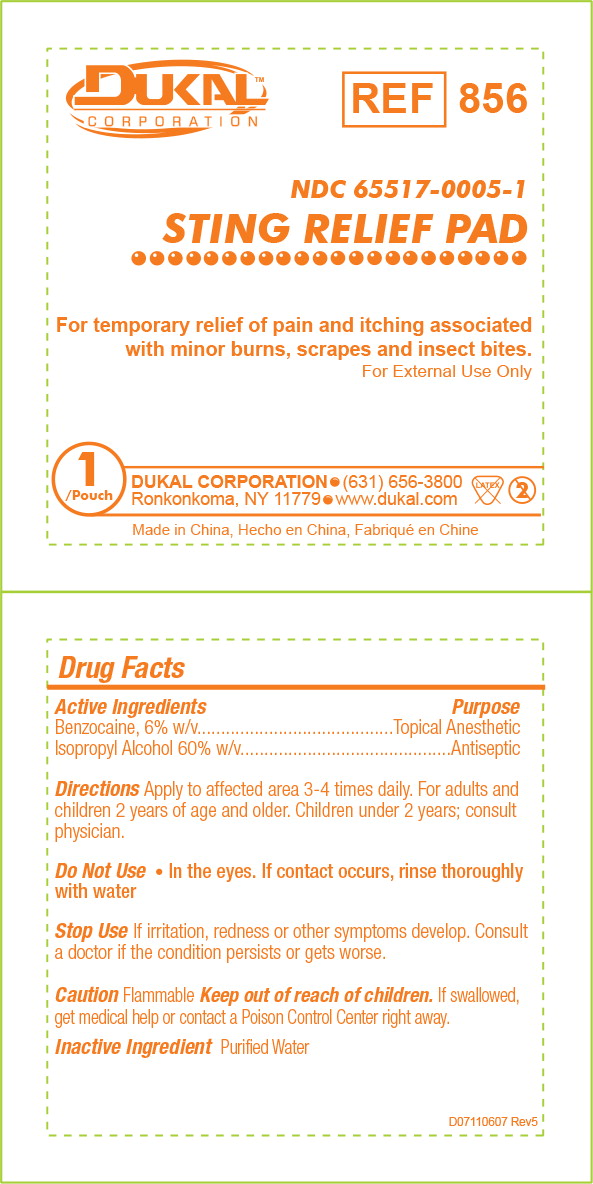 DRUG LABEL: DUKAL STING RELIEF PAD
NDC: 65517-0005 | Form: SWAB
Manufacturer: Dukal LLC
Category: otc | Type: HUMAN OTC DRUG LABEL
Date: 20231013

ACTIVE INGREDIENTS: BENZOCAINE
 60 mg/1 mL; ISOPROPYL ALCOHOL
 0.6 mL/1 mL
INACTIVE INGREDIENTS: WATER

Drug Facts

Active Ingredients

Benzocaine, 6% w/v

Isopropyl Alcohol 60% w/v

Purpose

Topical Anesthetic

Antiseptic

Directions

Apply to affected area 3-4 times daily. For adults and children 2 years of age and older. Children under 2 years; consult physician.

WARNINGS

Do Not Use

- In the eyes. If contact occurs, rinse thoroughly with water

Stop Use

If irritation, redness or other symptoms develop. Consult a doctor if the condition persists or gets worse.

Caution Flammable

Keep out of reach of children.

If swallowed, get medical help or contact a Poison Control Center right away.

Inactive Ingredient

Purified Water

D07110607 Rev5

Principal Display Panel - 0.4 mL Pouch Label

DUKAL™
CORPORATION

REF
856

NDC 65517-0005-1
STING RELIEF PAD

For temporary relief of pain and itching associated with minor burns, scrapes and insect bites.

For External Use Only

1 Pouch

DUKAL CORPORATION • (631) 656-3800
Ronkonkoma, New York • www.dukal.com

Made in China, Hecho en China, Fabriqué en Chine